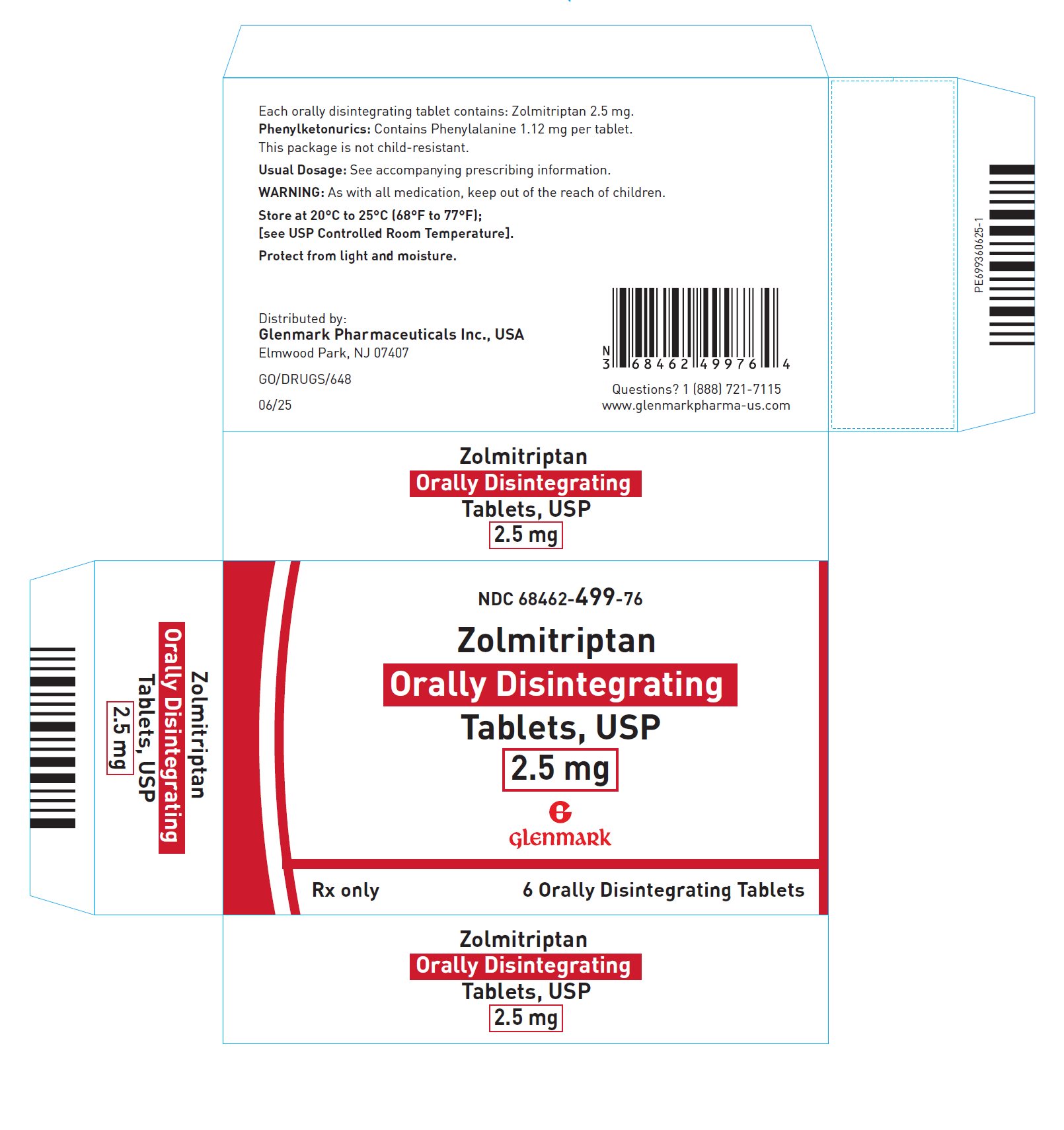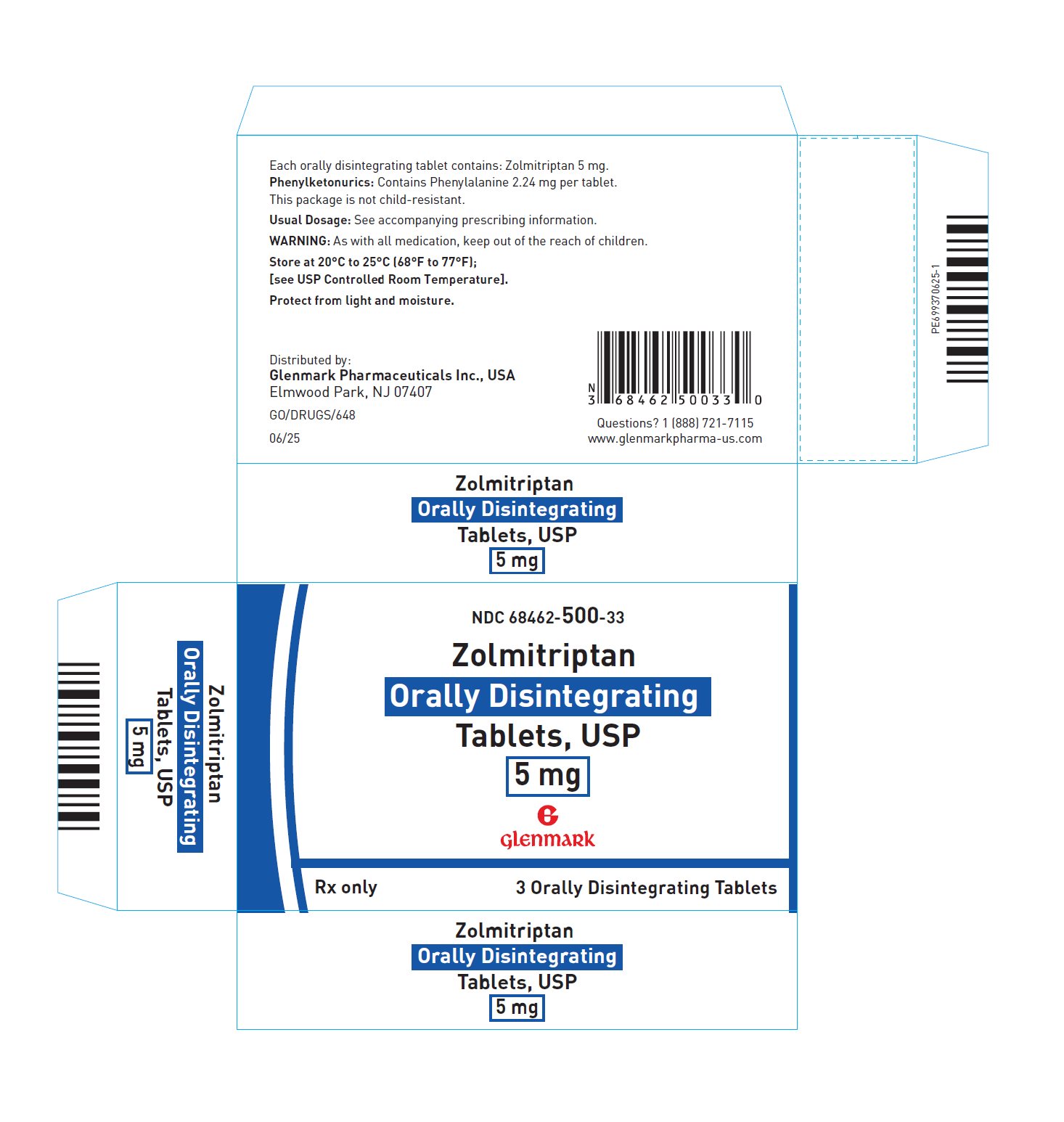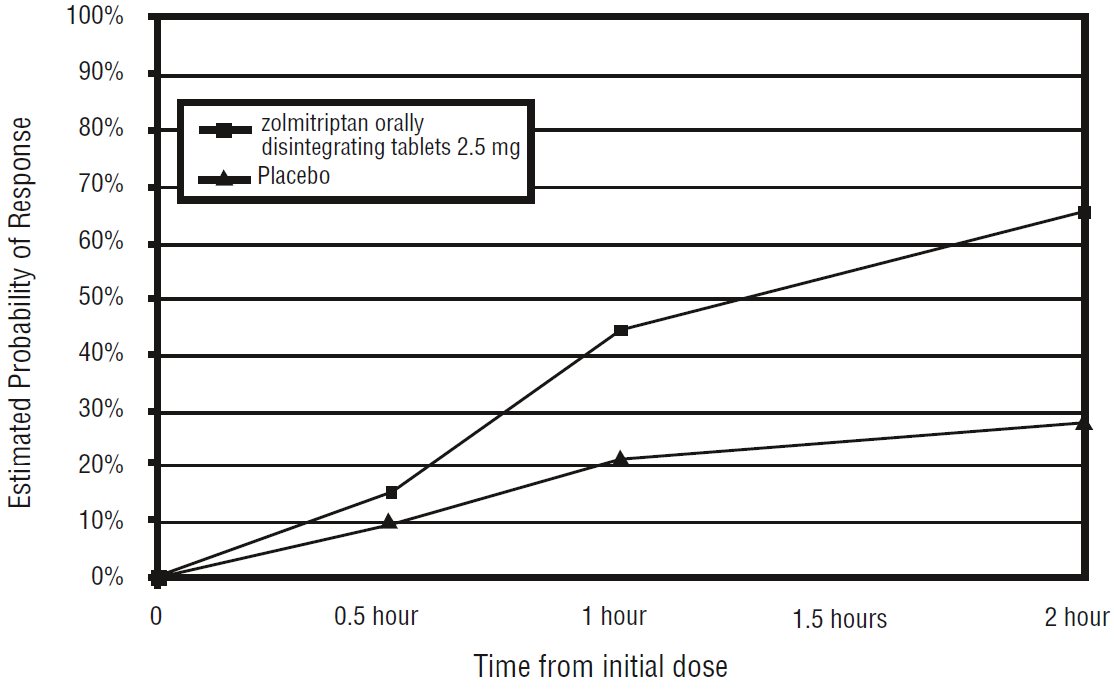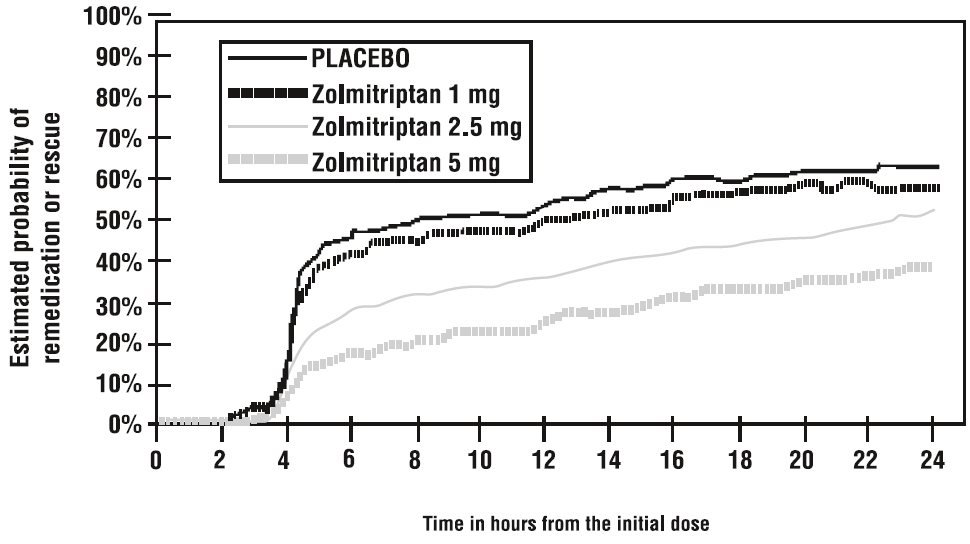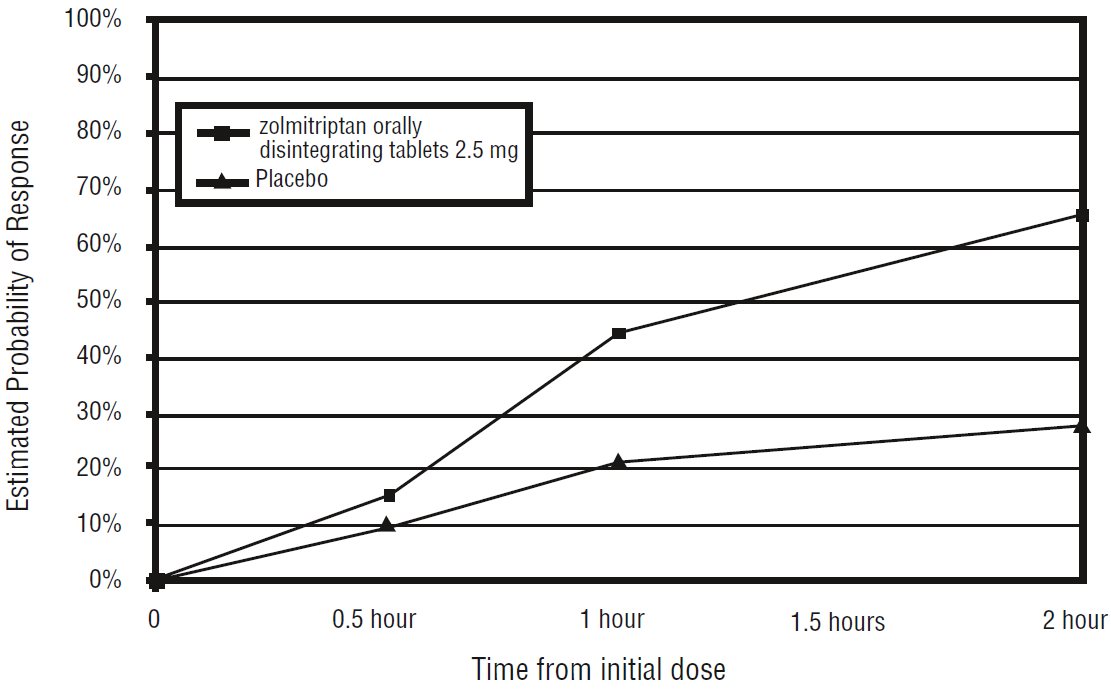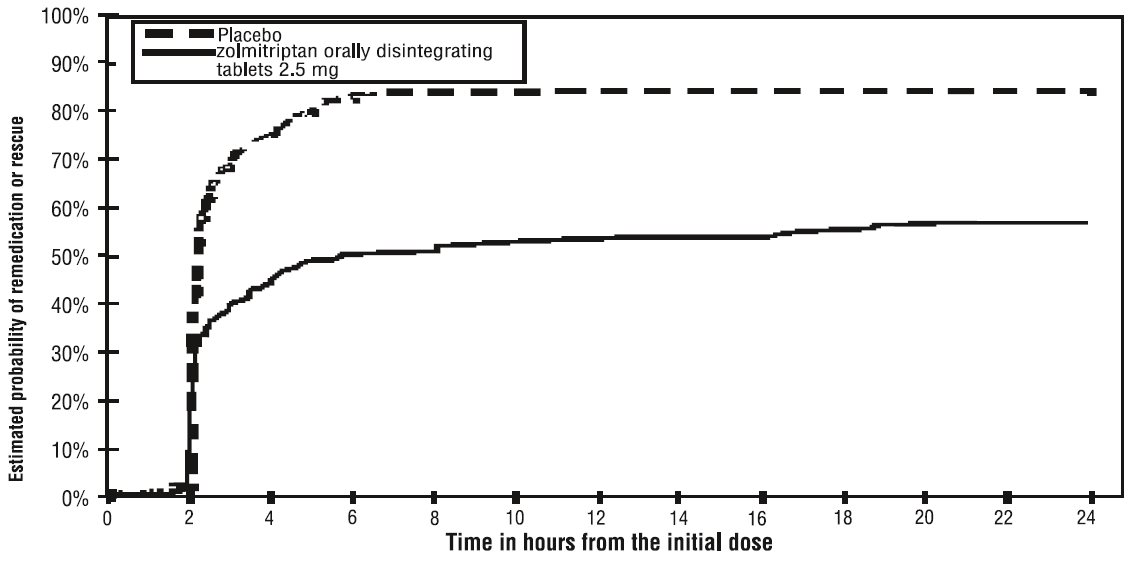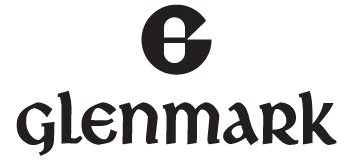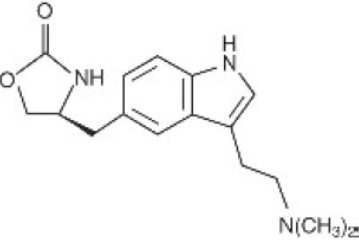 DRUG LABEL: zolmiptriptan
NDC: 68462-499 | Form: TABLET, ORALLY DISINTEGRATING
Manufacturer: Glenmark Pharmaceuticals Inc., USA
Category: prescription | Type: HUMAN PRESCRIPTION DRUG LABEL
Date: 20260129

ACTIVE INGREDIENTS: ZOLMITRIPTAN 2.5 mg/1 1
INACTIVE INGREDIENTS: MANNITOL; MICROCRYSTALLINE CELLULOSE; CROSPOVIDONE (120 .MU.M); ASPARTAME; SILICON DIOXIDE; TALC; MAGNESIUM STEARATE; STARCH, CORN

HIGHLIGHTS OF PRESCRIBING INFORMATION

These highlights do not include all the information needed to use ZOLMITRIPTAN ORALLY DISINTEGRATING TABLETS safely and effectively. See full prescribing information for ZOLMITRIPTAN ORALLY DISINTEGRATING TABLETS.
ZOLMITRIPTAN orally disintegrating tablets
Initial U.S. Approval: 1997

1 INDICATIONS AND USAGE

Zolmitriptan orally disintegrating tablets are a serotonin (5-HT)1B/1D receptor agonist (triptan) indicated for the acute treatment of migraine with or without aura in adults (1)

Limitations of Use:

- Use only after a clear diagnosis of migraine has been established (1)
- Not indicated for the prophylactic therapy of migraine (1)
- Not indicated for the treatment of cluster headache (1)

2 DOSAGE AND ADMINISTRATION

- Recommended starting dose: 1.25 mg or 2.5 mg (2.1)
- Maximum single dose: 5 mg (2.1)
- May repeat dose after 2 hours if needed; not to exceed 10 mg in any 24-hour period (2.1)
- Do not break zolmitriptan orally disintegrating tablets (2.2)
- Moderate or Severe Hepatic Impairment: 1.25 mg recommended (2.3, 8.6)

3 DOSAGE FORMS AND STRENGTHS

- Orally Disintegrating Tablets, USP: 2.5 mg and 5 mg (3)

4 CONTRAINDICATIONS

- History of coronary artery disease (CAD) or coronary vasospasm (4)
- Symptomatic Wolff-Parkinson-White Syndrome or other cardiac accessory conduction pathway disorders (4)
- History of stroke, transient ischemic attack, or hemiplegic or basilar migraine (4)
- Peripheral vascular disease (4)
- Ischemic bowel disease (4)
- Uncontrolled hypertension (4)
- Recent (within 24 hours) use of another 5-HT1 agonist (e.g., another triptan), or an ergotamine-containing medication (4)
- Monoamine oxidase (MAO)-A inhibitor used in past 2 weeks (4)
- Known hypersensitivity to zolmitriptan (4)

5 WARNINGS AND PRECAUTIONS

- Myocardial Ischemia/Infarction, and Prinzmetal Angina: Perform cardiac evaluation in patients with multiple cardiovascular risk factors (5.1)
- Arrhythmias: Discontinue zolmitriptan if occurs (5.2)
- Chest/Throat/Neck/Jaw Pain, Tightness, and Pressure: Generally not associated with myocardial ischemia; evaluate for CAD in patients at high risk (5.3)
- Cerebral Hemorrhage, Subarachnoid Hemorrhage, and Stroke: Discontinue zolmitriptan if occurs (5.4)
- Gastrointestinal Ischemic Reactions and Peripheral Vasospastic Reactions: Discontinue zolmitriptan if occurs (5.5)
- Medication Overuse Headache: Detoxification may be necessary (5.6)
- Serotonin Syndrome: Discontinue zolmitriptan if occurs (5.7, 7.4)
- Patients with Phenylketonuria: Zolmitriptan orally disintegrating tablets contain phenylalanine (5.9)

6 ADVERSE REACTIONS

Most common adverse reactions (≥ 5% and > placebo) were neck/throat/jaw pain/tightness/pressure, dizziness, paresthesia, asthenia, somnolence, warm/cold sensation, nausea, heaviness sensation, and dry mouth (6.1)

To report SUSPECTED ADVERSE REACTIONS, contact Glenmark Pharmaceuticals Inc., USA at 1 (888) 721-7115 or FDA at 1-800-FDA-1088 or www.fda.gov/medwatch.

8 USE IN SPECIFIC POPULATIONS

Pregnancy: Based on animal data, may cause fetal harm (8.1)

FULL PRESCRIBING INFORMATION

1 INDICATIONS AND USAGE

Zolmitriptan orally disintegrating tablets are indicated for the acute treatment of migraine with or without aura in adults.

Limitations of Use

- Only use zolmitriptan orally disintegrating tablets if a clear diagnosis of migraine has been established. If a patient has no response to zolmitriptan orally disintegrating tablets treatment for the first migraine attack, reconsider the diagnosis of migraine before zolmitriptan orally disintegrating tablets are administered to treat any subsequent attacks.
- Zolmitriptan orally disintegrating tablets are not indicated for the prevention of migraine attacks.
- Safety and effectiveness of zolmitriptan orally disintegrating tablets have not been established for cluster headache.

2 DOSAGE AND ADMINISTRATION

2.1 Dosing Information

The recommended starting dose of zolmitriptan orally disintegrating tablets is 1.25 mg or 2.5 mg. The 1.25 mg dose can be achieved by manually breaking the functionally-scored 2.5 mg tablet in half. The maximum recommended single dose of zolmitriptan orally disintegrating tablets is 5 mg.

In controlled clinical trials, a greater proportion of patients had headache response following a 2.5 mg or 5 mg dose than following a 1 mg dose. There was little added benefit from the 5 mg dose compared to the 2.5 mg dose, but adverse reactions were more frequent with the 5 mg dose.

If the migraine has not resolved by 2 hours after taking zolmitriptan orally disintegrating tablets, or returns after a transient improvement, a second dose may be administered at least 2 hours after the first dose. The maximum daily dose is 10 mg in any 24-hour period.

The safety of zolmitriptan orally disintegrating tablets in the treatment of an average of more than three migraines in a 30-day period has not been established.

2.2 Administration of Zolmitriptan Orally Disintegrating Tablets

Instruct patients not to break zolmitriptan orally disintegrating tablets because they are not functionally-scored. Administration with liquid is not necessary.

Orally disintegrating tablets are packaged in a blister pack. Instruct patients not to remove the tablet from the blister until just prior to dosing. Subsequently, instruct patients to peel the blister pack open, and to place the orally disintegrating tablet on the tongue, where it will dissolve and it will be swallowed with the saliva.

2.3 Dosing in Patients with Hepatic Impairment

The recommended dose of zolmitriptan orally disintegrating tablets in patients with moderate to severe hepatic impairment is 1.25 mg (one-half of one 2.5 mg zolmitriptan tablet) because of increased zolmitriptan blood levels in these patients and elevation of blood pressure in some of these patients. Limit the total daily dose in patients with severe hepatic impairment to no more than 5 mg per day.

The use of zolmitriptan orally disintegrating tablets is not recommended in patients with moderate or severe hepatic impairment because these orally disintegrating tablets should not be broken in half [see Use in Specific Populations (8.6), and Clinical Pharmacology (12.3)].

2.4 Dosing in Patients taking Cimetidine

If zolmitriptan orally disintegrating tablets are co-administered with cimetidine, limit the maximum single dose of zolmitriptan orally disintegrating tablets to 2.5 mg, not to exceed 5 mg in any 24-hour period [see Drug Interactions (7.5), Clinical Pharmacology (12.3)].

3 DOSAGE FORMS AND STRENGTHS

2.5 mg Zolmitriptan Orally Disintegrating Tablets, USP: White to off-white, round tablets debossed with ‘F7’ on one side and plain on the other side.

5 mg Zolmitriptan Orally Disintegrating Tablets, USP: White to off-white, round tablets debossed with ‘F11’on one side and plain on the other side.

4 CONTRAINDICATIONS

Zolmitriptan orally disintegrating tablets are contraindicated in patients with:

- Ischemic coronary artery disease (angina pectoris, history of myocardial infarction, or documented silent ischemia), other significant underlying cardiovascular disease, or coronary artery vasospasm including Prinzmetal’s angina [see Warnings and Precautions (5.1)].
- Wolff-Parkinson-White Syndrome or arrhythmias associated with other cardiac accessory conduction pathway disorders [see Warnings and Precautions (5.2)].
- History of stroke, transient ischemic attack (TIA), or history of hemiplegic or basilar migraine because these patients are at a higher risk of stroke [see Warnings and Precautions (5.4)].
- Peripheral vascular disease (PVD) [see Warnings and Precautions (5.5)].
- Ischemic bowel disease [see Warnings and Precautions (5.5)].
- Uncontrolled hypertension [see Warnings and Precautions (5.8)].
- Recent use (i.e., within 24 hours) of another 5-HT1 agonist, ergotamine-containing medication, or ergot-type medication (such as dihydroergotamine or methysergide) [see Drug Interactions (7.1, 7.3)].
- Concurrent administration of a monoamine oxidase (MAO)-A inhibitor or recent use of a MAO-A inhibitor (that is within 2 weeks) [see Drug Interactions (7.2) and Clinical Pharmacology (12.3)].
- Known hypersensitivity to zolmitriptan orally disintegrating tablets (angioedema and anaphylaxis seen) [see Adverse Reactions (6.2)].

5 WARNINGS AND PRECAUTIONS

5.1 Myocardial Ischemia, Myocardial Infarction, and Prinzmetal Angina

Zolmitriptan is contraindicated in patients with ischemic or vasospastic coronary artery disease (CAD). There have been rare reports of serious cardiac adverse reactions, including acute myocardial infarction, occurring within a few hours following administration of zolmitriptan. Some of these reactions occurred in patients without known CAD. 5-HT1agonists including zolmitriptan may cause coronary artery vasospasm (Prinzmetal Angina), even in patients without a history of CAD.

Perform a cardiovascular evaluation in triptan-naïve patients who have multiple cardiovascular risk factors (e.g., increased age, diabetes, hypertension, smoking, obesity, strong family history of CAD) prior to receiving zolmitriptan. Do not administer zolmitriptan if there is evidence of CAD or coronary artery vasospasm [see Contraindications (4)]. For patients with multiple cardiovascular risk factors who have a negative cardiovascular evaluation, consider administrating the first zolmitriptan dose in a medically-supervised setting and performing an electrocardiogram (ECG) immediately following zolmitriptan administration. For such patients, consider periodic cardiovascular evaluation in intermittent long-term users of zolmitriptan.

5.2 Arrhythmias

Life-threatening disturbances of cardiac rhythm including ventricular tachycardia and ventricular fibrillation leading to death have been reported within a few hours following the administration of 5-HT1 agonists. Discontinue zolmitriptan if these disturbances occur. Zolmitriptan is contraindicated in patients with Wolff-Parkinson-White Syndrome or arrhythmias associated with other cardiac accessory conduction pathway disorders [see Contraindications (4)].

5.3 Chest, Throat, Neck and Jaw Pain/Tightness/Pressure

As with other 5-HT1 agonists, sensations of tightness, pain, and pressure in the chest, throat, neck, and jaw commonly occur after treatment with zolmitriptan and is usually non-cardiac in origin. However, perform a cardiac evaluation if these patients are at high cardiac risk. 5-HT1 agonists including zolmitriptan are contraindicated in patients with CAD or Prinzmetal’s variant angina [see Contraindications (4)].

5.4 Cerebrovascular Events

Cerebral hemorrhage, subarachnoid hemorrhage, and stroke have occurred in patients treated with 5-HT1 agonists, and some have resulted in fatalities. In a number of cases, it appears possible that the cerebrovascular events were primary, the 5-HT1 agonist having been administered in the incorrect belief that the symptoms experienced were a consequence of migraine, when they were not.

As with other acute migraine therapies, before treating headaches in patients not previously diagnosed as migraineurs, and in migraineurs who present with symptoms atypical for migraine, exclude other potentially serious neurological conditions. Zolmitriptan is contraindicated in patients with a history of stroke or transient ischemic attack [see Contraindications (4)].

5.5 Other Vasospasm Reactions

5-HT1 agonists, including zolmitriptan, may cause non-coronary vasospastic reactions, such as peripheral vascular ischemia, gastrointestinal vascular ischemia and infarction (presenting with abdominal pain and bloody diarrhea), splenic infarction, and Raynaud’s syndrome. In patients who experience symptoms or signs suggestive of a vasospastic reaction following the use of any 5-HT1 agonist, rule out a vasospastic reaction before receiving additional zolmitriptan doses [see Contraindications (4)].

Reports of transient and permanent blindness and significant partial vision loss have been reported with the use of 5-HT1 agonists. Since visual disorders may be part of a migraine attack, a causal relationship between these events and the use of 5-HT1 agonists have not been clearly established.

5.6 Medication Overuse Headache

Overuse of acute migraine drugs (e.g., ergotamine, triptans, opioids, or a combination of drugs for 10 or more days per month) may lead to exacerbation of headache (medication overuse headache). Medication overuse headache may present as migraine-like daily headaches or as a marked increase in frequency of migraine attacks. Detoxification of patients, including withdrawal of the overused drugs, and treatment of withdrawal symptoms (which often includes a transient worsening of headache) may be necessary.

5.7 Serotonin Syndrome

Serotonin syndrome may occur with triptans, including zolmitriptan, particularly during co-administration with selective serotonin reuptake inhibitors (SSRIs), serotonin norepinephrine reuptake inhibitors (SNRIs), tricyclic antidepressants (TCAs), and MAO inhibitors [see Drug Interactions (7.5)]. Serotonin syndrome symptoms may include mental status changes (e.g., agitation, hallucinations, coma), autonomic instability (e.g., tachycardia, labile blood pressure, hyperthermia), neuromuscular aberrations (e.g., hyperreflexia, incoordination), and/or gastrointestinal symptoms (e.g., nausea, vomiting, diarrhea). The onset of symptoms usually rapidly occurs within minutes to hours of receiving a new or a greater dose of a serotonergic medication. Discontinue zolmitriptan if serotonin syndrome is suspected [see Drug Interactions (7.4)].

5.8 Increase in Blood Pressure

Significant elevations in systemic blood pressure have been reported in patients treated with 5-HT1 agonists including patients without a history of hypertension; very rarely, these increases in blood pressure have been associated with serious adverse reactions. In healthy subjects treated with 5 mg of zolmitriptan, an increase of 1 and 5 mm Hg in the systolic and diastolic blood pressure, respectively, was seen. In a study of patients with moderate to severe liver impairment, 7 of 27 patients experienced 20 to 80 mm Hg elevations in systolic and/or diastolic blood pressure after a dose of 10 mg of zolmitriptan. As with all triptans, blood pressure should be monitored in zolmitriptan-treated patients. Zolmitriptan is contraindicated in patients with uncontrolled hypertension [see Contraindications (4)].

5.9 Risks in Patients with Phenylketonuria

Phenylalanine can be harmful to patients with phenylketonuria (PKU). Zolmitriptan orally disintegrating tablets contain phenylalanine (a component of aspartame). Each 2.5 mg and 5 mg orally disintegrating tablet contains 1.12 and 2.24 mg of phenylalanine, respectively.

6 ADVERSE REACTIONS

The following adverse reactions are described elsewhere in other sections of the prescribing information:

- Myocardial Ischemia, Myocardial Infarction, and Prinzmetal Angina [see Warnings and Precautions (5.1)].
- Arrhythmias [see Warnings and Precautions (5.2)].
- Chest and or Throat, Neck and Jaw Pain/Tightness/Pressure [see Warnings and Precautions (5.3)].
- Cerebrovascular Events [see Warnings and Precautions (5.4)].
- Other Vasospasm Reactions [see Warnings and Precautions (5.5)].
- Medication Overuse Headache [see Warnings and Precautions (5.6)].
- Serotonin Syndrome [see Warnings and Precautions (5.7)].
- Increase in Blood Pressure [see Warnings and Precautions (5.8)].
- Risks in Patients with Phenylketonuria [see Warnings and Precautions (5.9)].

6.1 Clinical Trials Experience

Because clinical studies are conducted under widely varying conditions, adverse reaction rates observed in the clinical studies of a drug cannot be directly compared to rates in the clinical studies of another drug and may not reflect the rates observed in practice.

In a long-term, open-label study where patients were allowed to treat multiple migraine attacks for up to 1 year, 8% (167 out of 2,058) withdrew from the trial because of adverse reaction.

The most common adverse reactions (≥ 5% and > placebo) in these trials were neck/throat/jaw pain, dizziness, paresthesia, asthenia, somnolence, warm/cold sensation, nausea, heaviness sensation, and dry mouth.

Table 1 lists the adverse reactions that occurred in ≥2% of the 2,074 patients in any one of the zolmitriptan 1 mg, 2.5 mg, or 5 mg dose groups in the controlled clinical trials of zolmitriptan in patients with migraines (Studies 1, 2, 3, 4, and 5) [see Clinical Studies (14)]. Only adverse reactions that were at least 2% more frequent in a zolmitriptan group compared to the placebo group are included.

Several of the adverse reactions appear dose related, notably paresthesia, sensation of heaviness or tightness in chest, neck, jaw, and throat, dizziness, somnolence and possibly asthenia and nausea.

Table 1: Adverse Reaction Incidence in Five Pooled Placebo-Controlled Migraine Clinical Trials*

 | Placebo; (n=401) | Zolmitriptan 1 mg (n=163) | Zolmitriptan 2.5 mg (n=498) | Zolmitriptan 5 mg (n=1012)
ATYPICAL SENSATIONS | 6% | 12% | 12% | 18%
Paresthesia (all types) | 2% | 5% | 7% | 9%
Warm/cold sensation | 4% | 6% | 5% | 7%
PAIN AND PRESSURE SENSATIONS | 7% | 13% | 14% | 22%
Chest-pain/tightness/pressure and/or heaviness | 1% | 2% | 3% | 4%
Neck/throat/jaw-pain/tightness/pressure | 3% | 4% | 7% | 10%
Heaviness other than chest or neck | 1% | 1% | 2% | 5%
Other- Pressure/tightness/heaviness | 0% | 2% | 2% | 2%
DIGESTIVE | 8% | 11% | 16% | 14%
Dry mouth | 2% | 5% | 3% | 3%
Dyspepsia | 1% | 3% | 2% | 1%
Dysphagia | 0% | 0% | 0% | 2%
Nausea | 4% | 4% | 9% | 6%
NEUROLOGICAL | 10% | 11% | 17% | 21%
Dizziness | 4% | 6% | 8% | 10%
Somnolence | 3% | 5% | 6% | 8%
Vertigo | 0% | 0% | 0% | 2%
OTHER
Asthenia | 3% | 5% | 3% | 9%
Sweating | 1% | 0% | 2% | 3%

*Only adverse reactions that were at least 2% more frequent in a zolmitriptan group compared to the placebo group are included.

There were no differences in the incidence of adverse reactions in controlled clinical trials in the following subgroups: gender, weight, age, use of prophylactic medications, or presence of aura. There were insufficient data to assess the impact of race on the incidence of adverse reactions.

Less Common Adverse Reactions with Zolmitriptan Tablets:

In the paragraphs that follow, the frequencies of less commonly reported adverse clinical reactions are presented. Because the reports include reactions observed in open and uncontrolled studies, the role of zolmitriptan in their causation cannot be reliably determined. Furthermore, variability associated with adverse reaction reporting, the terminology used to describe adverse reactions, etc., limit the value of the quantitative frequency estimates provided. Adverse reaction frequencies were calculated as the number of patients who used zolmitriptan tablets and reported a reaction divided by the total number of patients exposed to zolmitriptan tablets (n=4,027). Reactions were further classified within body system categories and enumerated in order of decreasing frequency using the following definitions: infrequent adverse reactions (those occurring in 1/100 to 1/1,000 patients) and rare adverse reactions (those occurring in less than 1/1,000 patients).

General: Infrequent were allergic reactions.

Cardiovascular: Infrequent were arrhythmias, hypertension, and syncope. Rare was tachycardia.

Neurological: Infrequent were agitation, anxiety, depression, emotional lability and insomnia; Rare were amnesia, hallucinations, and cerebral ischemia.

Skin: Infrequent were pruritus, rash and urticaria.

Urogenital: Infrequent were polyuria, urinary frequency and urinary urgency.

Adverse Reactions with Zolmitriptan Orally Disintegrating Tablets

The adverse reaction profile seen with zolmitriptan orally disintegrating tablets was similar to that seen with zolmitriptan tablets.

6.2 Postmarketing Experience

The following adverse reactions were identified during post approval use of zolmitriptan. Because these reactions are reported voluntarily from a population of uncertain size, it is not always possible to reliably estimate their frequency or establish a causal relationship to drug exposure.

The reactions enumerated include all except those already listed in the Clinical Trials Experience section above or the Warnings and Precautions section.

Hypersensitivity Reactions:

As with other 5-HT1B/1D agonists, there have been reports of anaphylaxis, anaphylactoid, and hypersensitivity reactions including angioedema in patients receiving zolmitriptan. Zolmitriptan is contraindicated in patients with a history of hypersensitivity reaction to zolmitriptan.

7 DRUG INTERACTIONS

7.1 Ergot-containing Drugs

Ergot-containing drugs have been reported to cause prolonged vasospastic reactions. Because these effects may be additive, use of ergotamine-containing or ergot-type medications (like dihydroergotamine or methysergide) and zolmitriptan within 24 hours of each other is contraindicated [see Contraindications (4)].

7.2 MAO-A Inhibitors

MAO-A inhibitors increase the systemic exposure of zolmitriptan and its active N-desmethyl metabolite. Therefore, the use of zolmitriptan in patients receiving MAO-A inhibitors is contraindicated [see Contraindications (4), Clinical Pharmacology (12.3)].

7.3 5-HT1B/1D agonists

Concomitant use of other 5-HT1B/1D agonists (including triptans) within 24 hours of zolmitriptan treatment is contraindicated because the risk of vasospastic reactions may be additive [see Contraindications (4)].

7.4 Selective Serotonin Reuptake Inhibitors and Serotonin Norepinephrine Reuptake Inhibitors

Cases of life-threatening serotonin syndrome have been reported during co-administration of triptans and selective serotonin reuptake inhibitors (SSRIs) or serotonin norepinephrine reuptake inhibitors (SNRIs) [see Warnings and Precautions (5.7)].

7.5 Cimetidine

Following administration of cimetidine, the half-life and blood levels of zolmitriptan and its active N-desmethyl metabolite were approximately doubled [see Clinical Pharmacology (12.3)]. If cimetidine and zolmitriptan are used concomitantly, limit the maximum single dose of zolmitriptan to 2.5 mg, not to exceed 5 mg in any 24-hour period [see Dosage and Administration (2.4), Clinical Pharmacology (12.3)].

8 USE IN SPECIFIC POPULATIONS

8.1 Pregnancy

Risk Summary

There are no adequate data on the developmental risk associated with the use of zolmitriptan in pregnant women. In reproductive toxicity studies in rats and rabbits, oral administration of zolmitriptan to pregnant animals resulted in embryolethality and fetal abnormalities (malformations and variations) at clinically relevant exposures (see Data).

In the U.S. general population, the estimated background risk of major birth defects and miscarriage in clinically recognized pregnancies is 2% to 4% and 15% to 20%, respectively. The estimated rates of major birth defects (2.2% to 2.9%) and miscarriage (17%) among deliveries to women with migraine are similar to rates reported in women without migraine.

Clinical Considerations

Disease-Associated Maternal and/or Embryo/Fetal Risk

Published data have suggested that women with migraine may be at increased risk of preeclampsia during pregnancy.

Data

Animal Data

When zolmitriptan was administered to pregnant rats during the period of organogenesis at oral doses of 100, 400, and 1200 mg/kg/day (plasma exposures (AUCs) ≈280, 1100, and 5000 times the human AUC at the maximum recommended human dose (MRHD) of 10 mg/day), there was a dose-related increase in embryolethality. A no-effect dose for embryolethality was not established. When zolmitriptan was administered to pregnant rabbits during the period of organogenesis at oral doses of 3, 10, and 30 mg/kg/day (plasma AUCs ≈1, 11, and 42 times the human AUC at the MRHD), there were increases in embryolethality and in fetal malformations and variations. The no-effect dose for adverse effects on embryofetal development was associated with a plasma AUC similar to that in humans at the MRHD. When female rats were given zolmitriptan during gestation, parturition, and lactation at oral doses of 25, 100, and 400 mg/kg/day (plasma AUCs ≈70, 280, and 1100 times that in human at the MRHD), an increased incidence of hydronephrosis was found in the offspring. The no-effect dose was associated with a plasma AUC ≈280 times that in humans at the MRHD.

8.2 Lactation

Risk Summary

There are no data on the presence of zolmitriptan or its metabolites in human milk, the effects on the breastfed infant, or the effects of zolmitriptan and its metabolites on milk production. In rats, oral dosing with zolmitriptan resulted in levels in milk up to 4 times that in maternal plasma.

The developmental and health benefits of breastfeeding should be considered along with the mother’s clinical need for zolmitriptan and any potential adverse effects on the breastfed infant from zolmitriptan or from the underlying maternal condition.

8.4 Pediatric Use

The safety and effectiveness in pediatric patients have not been established. Therefore, zolmitriptan is not recommended for use in patients under 18 years of age.

One randomized, placebo-controlled clinical trial of zolmitriptan tablets (2.5, 5 and 10 mg) evaluated 696 pediatric patients (aged 12 to 17 years) with migraines. This study did not demonstrate the efficacy of zolmitriptan compared to placebo in the treatment of migraine in adolescents. Adverse reactions in the adolescent patients treated with zolmitriptan were similar in nature and frequency to those reported in clinical trials in adults treated with zolmitriptan. Zolmitriptan has not been studied in pediatric patients less than 12 years old.

In the postmarketing experience with triptans, including zolmitriptan, there were no additional adverse reactions seen in pediatric patients that were not seen in adults.

8.5 Geriatric Use

Clinical studies of zolmitriptan did not include sufficient numbers of subjects aged 65 and over to determine whether they respond differently from younger subjects. Other reported clinical experience has not identified differences in responses between the elderly and younger patients. In general, dose selection for an elderly patient should be cautious, usually starting at the low end of the dosing range, reflecting the greater frequency of decreased hepatic, renal, or cardiac function, and of concomitant disease or other drug therapy.

A cardiovascular evaluation is recommended for geriatric patients who have other cardiovascular risk factors (e.g., diabetes, hypertension, smoking, obesity, strong family history of coronary artery disease) prior to receiving zolmitriptan [see Warnings and Precautions (5.1)].

The pharmacokinetics of zolmitriptan were similar in geriatric patients (aged > 65 years) compared to younger patients [see Clinical Pharmacology (12.3)].

8.6 Patients with Hepatic Impairment

After oral zolmitriptan administration, zolmitriptan blood levels were increased in patients with moderate to severe hepatic impairment, and significant elevation in blood pressure was observed in some of these patients [see Warnings and Precautions (5.8)]. Therefore, adjust the zolmitriptan dose and administer with caution in patients with moderate or severe hepatic impairment [see Dosage and Administration (2.3), Clinical Pharmacology (12)].

10 OVERDOSAGE

There is no experience with acute overdose of zolmitriptan. Clinical study subjects who received single 50 mg oral doses of zolmitriptan commonly experienced sedation.

There is no specific antidote to zolmitriptan. In cases of severe intoxication, intensive care procedures are recommended, including establishing and maintaining a patent airway, ensuring adequate oxygenation and ventilation, and monitoring and support of the cardiovascular system.

The elimination half-life of zolmitriptan is 3 hours [see Clinical Pharmacology (12.1)]; therefore, monitor patients after overdose with zolmitriptan for at least 15 hours or until symptoms or signs resolve. It is unknown what effect hemodialysis or peritoneal dialysis has on the plasma concentrations of zolmitriptan.

11 DESCRIPTION

Zolmitriptan Orally Disintegrating Tablets, USP contain zolmitriptan, which is a selective 5-hydroxytryptamine1B/1D (5-HT1B/1D) receptor agonist. Zolmitriptan is chemically designated as (4S)-4-[[3-[2-(dimethylamino)ethyl]-1H-indol-5-yl]methyl]-2-oxazolidinone and has the following chemical structure:

The molecular formula is C16H21N3O2, representing a molecular weight of 287.36 g/mol. Zolmitriptan is a white to off-white powder that is soluble in methanol and acetone; insoluble in water.

Zolmitriptan Orally Disintegrating Tablets, USP are available as 2.5 mg and 5 mg white uncoated tablets for oral administration. The orally disintegrating tablets contain aspartame [see Warnings and Precautions (5.9)], colloidal silicon dioxide, crospovidone, magnesium stearate, mannitol, microcrystalline cellulose, peppermint flavor and talc. The peppermint flavor contains corn starch.

12 CLINICAL PHARMACOLOGY

12.1 Mechanism of Action

Zolmitriptan binds with high affinity to human recombinant 5-HT1D and 5-HT1B receptors, and moderate affinity for 5-HT1A receptors. The N-desmethyl metabolite also has high affinity for 5-HT1B/1D and moderate affinity for 5-HT1A receptors.

Migraines are likely due to local cranial vasodilatation and/or to the release of sensory neuropeptides (vasoactive intestinal peptide, substance P and calcitonin gene-related peptide) through nerve endings in the trigeminal system. The therapeutic activity of zolmitriptan for the treatment of migraine headache is thought to be due to the agonist effects at the 5-HT1B/1D receptors on intracranial blood vessels (including the arterio-venous anastomoses) and sensory nerves of the trigeminal system which result in cranial vessel constriction and inhibition of pro-inflammatory neuropeptide release.

12.3 Pharmacokinetics

Absorption, Distribution, Metabolism, and Excretion

Absorption

Zolmitriptan is well absorbed after oral administration for both zolmitriptan tablets and zolmitriptan orally disintegrating tablets. Zolmitriptan displays linear kinetics over the dose range of 2.5 to 50 mg.

The AUC and Cmax of zolmitriptan are similar following administration of zolmitriptan tablets and zolmitriptan orally disintegrating tablets, but the Tmax is somewhat later with zolmitriptan orally disintegrating tablets, with a median Tmax of 3 hours for zolmitriptan orally disintegrating tablet compared with 1.5 hours for the zolmitriptan tablet. The AUC, Cmax, and Tmax for the active N-desmethyl metabolite are similar for the two formulations.

During a moderate to severe migraine attack, mean AUC0 to 4 and Cmax for zolmitriptan, dosed as a zolmitriptan tablet, were decreased by 40% and 25%, respectively, and mean Tmax was delayed by one-half hour compared to the same patients during a migraine free period.

Food has no significant effect on the bioavailability of zolmitriptan. No accumulation occurred on multiple dosing.

Distribution

Mean absolute bioavailability is approximately 40%. The mean apparent volume of distribution is 7 L/kg. Plasma protein binding of zolmitriptan is 25% over the concentration range of 10 to 1000 ng/mL.

Metabolism

Zolmitriptan is converted to an active N-desmethyl metabolite; the metabolite concentrations are about two-thirds that of zolmitriptan. Because the 5HT1B/1D potency of the metabolite is 2 to 6 times that of the parent compound, the metabolite may contribute a substantial portion of the overall effect after zolmitriptan administration.

Excretion

Total radioactivity recovered in urine and feces was 65% and 30% of the administered dose, respectively. About 8% of the dose was recovered in the urine as unchanged zolmitriptan. Indole acetic acid metabolite accounted for 31% of the dose, followed by N-oxide (7%) and N-desmethyl (4%) metabolites. The indole acetic acid and N-oxide metabolites are inactive.

Mean total plasma clearance is 31.5 mL/min/kg, of which one-sixth is renal clearance. The renal clearance is greater than the glomerular filtration rate suggesting renal tubular secretion.

Specific Populations

Hepatic Impairment

In patients with severe hepatic impairment, the mean Cmax, Tmax, and AUC0 to ∞ of zolmitriptan were increased 1.5-fold, 2-fold (2 vs. 4 hours), and 3-fold, respectively, compared to subjects with normal hepatic function. Seven out of 27 patients experienced 20 to 80 mm Hg elevations in systolic and/or diastolic blood pressure after a 10 mg zolmitriptan dose. Adjust the zolmitriptan dose in patients with moderate or severe hepatic impairment [see Dosage and Administration (2.3), Use in Specific Populations (8.6)].

Renal Impairment

Clearance of zolmitriptan was reduced by 25% in patients with severe renal impairment (Clcr ≥ 5 ≤ 25 mL/min) compared to subjects with normal renal function (Clcr > = 70 mL/min); no significant change in clearance was observed in patients with moderate renal impairment (Clcr ≥ 26 ≤ 50 mL/min).

Age

Zolmitriptan pharmacokinetics in healthy elderly non-migraineur volunteers (age 65 to 76 years) was similar to those in younger non-migraineur volunteers (age 18 to 39 years).

Sex

Mean plasma concentrations of zolmitriptan were up to 1.5-fold higher in females than males.

Race

Retrospective analysis of pharmacokinetic data between Japanese and Caucasians revealed no significant differences.

Hypertensive Patients

No differences in the pharmacokinetics of zolmitriptan or its effects on blood pressure were seen in mild to moderate hypertensive volunteers compared with normotensive controls.

Drug Interaction Studies

All drug interaction studies were performed in healthy volunteers using a single 10 mg dose of zolmitriptan and a single dose of the other drug except where otherwise noted.

MAO Inhibitors

Following one week of administration of moclobemide (150 mg twice daily), a specific MAO-A inhibitor, there was an increase of about 25% in both Cmax and AUC for zolmitriptan and a 3-fold increase in the Cmax and AUC of the active N-desmethyl metabolite of zolmitriptan. MAO inhibitors are contraindicated in zolmitriptan-treated patients [see Contraindications (4), Warnings and Precautions (5.7), Drug Interactions (7.2, 7.4)].

Selegiline, a selective MAO-B inhibitor, at a dose of 10 mg/day for 1 week, had no effect on the pharmacokinetics of zolmitriptan and its metabolite.

Cimetidine

Following the administration of cimetidine, the half-life and AUC of zolmitriptan (5 mg dose), and its active metabolite, were approximately doubled [see Dosage and Administration (2.4), Drug Interactions (7.5)].

Fluoxetine

The pharmacokinetics of zolmitriptan, as well as its effect on blood pressure, were unaffected by 4 weeks of pretreatment with oral fluoxetine (20 mg/day).

Propranolol

Cmax and AUC of zolmitriptan were increased 1.5-fold after one week of dosing with propranolol (160 mg/day). Cmax and AUC of the N-desmethyl metabolite were reduced by 30% and 15%, respectively. There were no changes in blood pressure or pulse rate following administration of propranolol with zolmitriptan.

Acetaminophen

A single 1 gram dose of acetaminophen did not alter the pharmacokinetics of zolmitriptan and its N-desmethyl metabolite. However, zolmitriptan administration delayed the Tmax of acetaminophen by one hour.

Metoclopramide

A single 10 mg dose of metoclopramide had no effect on the pharmacokinetics of zolmitriptan or its metabolites.

Oral Contraceptives

Retrospective analysis of pharmacokinetic data across studies indicated that mean Cmax and AUC of zolmitriptan were increased by 30% and 50%, respectively, and Tmax was delayed by one-half hour in women taking oral contraceptives. The effect of zolmitriptan on the pharmacokinetics of oral contraceptives has not been studied.

13 NONCLINICAL TOXICOLOGY

13.1 Carcinogenesis, Mutagenesis, Impairment of Fertility

Carcinogenesis

Zolmitriptan was administered to mice and rats at doses up to 400 mg/kg/day. Mice were dosed for 85 weeks (males) and 92 weeks (females); rats were dosed for 101 weeks (males) and 86 weeks (females). There was no evidence of drug-induced tumors in mice at plasma exposures (AUC) up to approximately 700 times that in humans at the maximum recommended human dose (MRHD) of 10 mg/day. In rats, there was an increase in the incidence of thyroid follicular cell hyperplasia and thyroid follicular cell adenomas in male rats receiving 400 mg/kg/day. No increase in tumors was observed in rats at 100 mg/kg/day, a dose associated with a plasma AUC approximately 700 times that in humans at the MRHD.

Mutagenesis

Zolmitriptan was positive in an in vitro bacterial reverse mutation (Ames) assay and in an in vitro chromosomal aberration assay in human lymphocytes. Zolmitriptan was negative in an in vitro mammalian gene cell mutation (CHO/HGPRT) assay and in oral in vivo mouse micronucleus assays in mouse and rat.

Impairment of Fertility

Studies of male and female rats administered zolmitriptan prior to and during mating and up to implantation showed no impairment of fertility at oral doses up to 400 mg/kg/day. The plasma exposure (AUC) at this dose was approximately 3000 times that in humans at the MRHD.

14 CLINICAL STUDIES

Zolmitriptan Tablets

The efficacy of zolmitriptan tablets in the acute treatment of migraine headaches was demonstrated in five randomized, double-blind, placebo-controlled studies (Studies 1, 2, 3, 4, and 5), of which two utilized the 1 mg dose, two utilized the 2.5 mg dose and four utilized the 5 mg dose. In Study 1, patients treated their headaches in a clinic setting. In the other studies, patients treated their headaches as outpatients. In Study 4, patients who had previously used sumatriptan were excluded, whereas in the other studies no such exclusion was applied.

Patients enrolled in these 5 studies were predominantly female (82%) and Caucasian (97%) with a mean age of 40 years (range 12 to 65). Patients were instructed to treat a moderate to severe headache. Headache response, defined as a reduction in headache severity from moderate or severe pain to mild or no pain, was assessed at 1, 2, and, in most studies, 4 hours after dosing. Associated symptoms such as nausea, photophobia, and phonophobia were also assessed. Maintenance of response was assessed for up to 24 hours post-dose. A second dose of zolmitriptan tablets or other medication was allowed 2 to 24 hours after the initial treatment for persistent and recurrent headache. The frequency and time to use of these additional treatments were also recorded. In all studies, the effect of zolmitriptan was compared to placebo in the treatment of a single migraine attack.

In all five studies, the percentage of patients achieving headache response 2 hours after treatment was significantly greater among patients who received zolmitriptan tablets at all doses (except for the 1 mg dose in the smallest study) compared to those who received placebo. In Studies 1 and 3, there was a statistically significant greater percentage of patients with headache response at 2 hours in the higher dose groups (2.5 and/or 5 mg) compared to the 1 mg dose group. There were no statistically significant differences between the 2.5 and 5 mg dose groups (or of doses up to 20 mg) for the primary end point of headache response at 2 hours in any study. The results of these controlled clinical studies are summarized in Table 2.

Table 2: Percentage of Patients with Headache Response (Reduction in Headache Severity from Moderate or Severe Pain to Mild or No Headache) 2 Hours Following Treatment in Studies 1 through 5

 | Placebo | Zolmitriptan 1 mg | Zolmitriptan 2.5 mg | Zolmitriptan 5 mg
Study 1* | 16% (n†=19) | 27% (n=22) | NA‡ | 60%§¶ (n=20)
Study 2 | 19% (n=88) | NA | NA | 66%§ (n=179)
Study 3 | 34% (n=121) | 50%§ (n=140) | 65%§¶; (n=260) | 67%§¶; (n=245)
Study 4# | 44%; (n=55) | NA | NA | 59%§; (n=491)
Study 5 | 36%; (n=92) | NA | 62%§; (n=178) | NA

*Study 1 was the only study in which patients treated the headache in a clinic setting.

† n=number of patients randomized

‡ NA = not applicable

§ P<0.05 in comparison with placebo.

¶ P<0.05 in comparison with 1 mg.

# Study 4 was the only study where patients were excluded who had previously used sumatriptan.

The estimated probability of achieving an initial headache response by 4 hours following treatment in pooled Studies 2, 3, and 5 is depicted in Figure 1.

Figure 1 Estimated Probability of Achieving Initial Headache Response (Reduction in Headache Severity from Moderate or Severe Pain to Mild or No Headache) Within 4 Hours of Treatment in Pooled Studies 2, 3, and 5*

*In this Kaplan-Meier plot, the averages displayed are based on pooled data from 3 placebo controlled, outpatient trials. Patients not achieving headache response or taking additional treatment prior to 4 hours were censored at 4 hours.

For patients with migraine associated photophobia, phonophobia, and nausea at baseline, there was a decreased incidence of these symptoms following administration of zolmitriptan tablets as compared with placebo.

Two to 24 hours following the initial dose of study treatment, patients were allowed to use additional treatment for pain relief in the form of a second dose of study treatment or other medication. The estimated probability of patients taking a second dose or other medication for migraine over the 24 hours following the initial dose of study treatment is summarized in Figure 2.

Figure 2 The Estimated Probability of Patients Taking a Second Dose or Other Medication for Migraines over the 24 Hours Following the Initial Dose of Study Treatment in Pooled Studies 2, 3, and 5*

*In this Kaplan-Meier plot, patients not using additional treatments were censored at 24 hours. The plot includes both patients who had headache response at 2 hours and those who had no response to the initial dose. The studies did not allow taking additional doses of study medication within 2 hours post-dose.

The efficacy of zolmitriptan was unaffected by presence of aura; duration of headache prior to treatment; relationship to menses; gender, age, or weight of the patient; pre-treatment nausea or concomitant use of common migraine prophylactic drugs.

Zolmitriptan Orally Disintegrating Tablets

The efficacy of zolmitriptan 2.5 mg orally disintegrating tablets was demonstrated in a randomized, placebo-controlled trial (Study 6) that was similar in design to the trials of zolmitriptan tablets. Patients were instructed to treat a moderate to severe headache. Of the 471 patients treated in Study 6, 87% were female and 97% were Caucasian, with a mean age of 41 years (range 18 to 62).

At 2 hours post-dosing, there was a statistically significant greater percentage of patients treated with zolmitriptan orally disintegrating tablets 2.5 mg with a headache response (reduction in headache severity from moderate or severe pain to mild or no headache) compared to patients treated with placebo (63% vs. 22%). The estimated probability of achieving an initial headache response by 2 hours following treatment with zolmitriptan orally disintegrating tablets is depicted in Figure 3.

Figure 3 Estimated Probability of Achieving Initial Headache Response (Reduction in Headache Severity from Moderate or Severe Pain to Mild or No Headache) Within 2 Hours in Study 6*

*In this Kaplan-Meier plot, patients taking additional treatment or not achieving headache response prior to 2 hours were censored at 2 hours.

For patients with migraine-associated photophobia, phonophobia and nausea at baseline, there was a decreased incidence of these symptoms following administration of zolmitriptan orally disintegrating tablets as compared to placebo.

Two to 24 hours following the initial dose of study treatment, patients were allowed to use additional treatment in the form of a second dose of study treatment or other medication. The estimated probability of patients taking a second dose or other medication for migraine over the 24 hours following the initial dose of study treatment in Study 6 is summarized in Figure 4.

Figure 4 The Estimated Probability of Patients Taking a Second Dose or Other Medication for Migraines over the 24 Hours Following the Initial Dose of Study Treatment in Study 6*

* In this Kaplan-Meier plot patients not taking additional treatments were censored at 24 hours. The plot includes both patients who had headache response at 2 hours and those who had no response to the initial dose. Taking another dose of study medication was allowed 2 hours post-dose in Study 6. In contrast to studies of zolmitriptan tablets (Studies 1, 2, 3, 4, and 5), Study 6 allowed re-dosing of zolmitriptan oral disintegrating tablets prior to 4 hours.

16 HOW SUPPLIED/STORAGE AND HANDLING

Zolmitriptan Orally Disintegrating Tablets, USP 2.5 mg - White to off-white, round tablets debossed with ‘F7’ on one side and plain on the other side are supplied in cartons (NDC 68462-499-76) containing a blister pack of 6 unit dose tablets (NDC 68462-499-40).

Zolmitriptan Orally Disintegrating Tablets, USP 5 mg - White to off-white, round tablets debossed with ‘F11’ on one side and plain on the other side are supplied in cartons (NDC 68462-500-33) containing a blister pack of 3 unit dose tablets (NDC 68462-500-40).

Store zolmitriptan orally disintegrating tablets at 20°C to 25°C (68°F to 77°F); [see USP Controlled Room

Temperature]. Protect from light and moisture.

17 PATIENT COUNSELING INFORMATION

Advise the patient to read the FDA-approved patient labeling (Patient Information).

Myocardial Ischemia and/or Infarction, Prinzmetal’s Angina, Other Vasospastic Reactions, and Cerebrovascular Events

Inform patients that zolmitriptan may cause serious cardiovascular adverse reactions such as myocardial infarction or stroke, which may result in hospitalization and even death. Although serious cardiovascular reactions can occur without warning symptoms, instruct patients to be alert for the signs and symptoms of chest pain, shortness of breath, weakness, slurring of speech, and instruct them to ask for medical advice when observing any indicative sign or symptoms. Instruct patients to seek medical advice if they have symptoms of other vasospastic reactions [see Warnings and Precautions (5.1, 5.2, 5.4, 5.5)].

Medication Overuse Headache

Inform patients that use of drugs to treat acute migraines for 10 or more days per month may lead to an exacerbation of headache, and encourage patients to record headache frequency and drug use (e.g., by keeping a headache diary) [see Warnings and Precautions (5.6)].

Serotonin Syndrome

Inform patients about the risk of serotonin syndrome with the use of zolmitriptan or other triptans, particularly during combined use with selective serotonin reuptake inhibitors (SSRIs) or serotonin norepinephrine reuptake inhibitors (SNRIs) [see Warnings and Precautions (5.7)].

Pregnancy

Advise patients to notify their healthcare provider if they are pregnant or plan to become pregnant.

Lactation

Advise patients to notify their healthcare provider if they are breastfeeding or plan to breastfeed [see Use in Specific Populations (8.2)].

Handling of Zolmitriptan Orally Disintegrating Tablets

Inform patients not to break zolmitriptan orally disintegrating tablets. Inform patients that the orally disintegrating tablet is packaged in a blister. Instruct patients not to remove the orally disintegrating tablet from the blister until just prior to dosing. Instruct patients that prior to dosing, peel open the blister pack and place the orally disintegrating tablet on the tongue, where it will dissolve and be swallowed with the saliva [see Dosage and Administration (2.2)].

Patients with Phenylketonuria

Inform patients with phenylketonuria (PKU) that zolmitriptan orally disintegrating tablets contain phenylalanine (a component of aspartame) [see Warnings and Precautions (5.9)].

Distributed by:

Glenmark Pharmaceuticals Inc., USA

Elmwood Park, NJ 07407

Questions? 1 (888) 721-7115

www.glenmarkpharma-us.com

June 2025

Patient Information

Zolmitriptan (ZOLE-mi-TRIP-tan)
Orally Disintegrating Tablets, USP

Please read this information before you start taking zolmitriptan orally disintegrating tablets and each time you renew your prescription just in case anything has changed. Remember, this summary does not take the place of discussions with your doctor. You and your doctor should discuss zolmitriptan orally disintegrating tablets when you start taking your medication and at regular checkups.

What are zolmitriptan orally disintegrating tablets?

Zolmitriptan orally disintegrating tablets are a prescription medication used to treat migraine headaches in adults. Zolmitriptan orally disintegrating tablets are not for other types of headaches. The safety and efficacy of zolmitriptan orally disintegrating tablets in patients under 18 have not been established.

What is a Migraine Headache?

Migraine is an intense, throbbing headache. You may have pain on one or both sides of your head. You may have nausea and vomiting, and be sensitive to light and noise. The pain and symptoms of a migraine headache can be worse than a common headache. Some women get migraines around the time of their menstrual period. Some people have visual symptoms before the headache, such as flashing lights or wavy lines, called an aura.

How do zolmitriptan orally disintegrating tablets work?

Treatment with zolmitriptan orally disintegrating tablets reduces swelling of blood vessels surrounding the brain. This swelling is associated with the headache pain of a migraine attack. Zolmitriptan orally disintegrating tablets block the release of substances from nerve endings that cause more pain and other symptoms like nausea, and sensitivity to light and sound. It is thought that these actions contribute to relief of your symptoms by zolmitriptan orally disintegrating tablets.

Who should not take zolmitriptan orally disintegrating tablets?

Do not take zolmitriptan orally disintegrating tablets if you:

- Have heart disease or a history of heart disease
- Have uncontrolled high blood pressure
- Have hemiplegic or basilar migraine (if you are not sure about this, ask your doctor)
- Have or had a stroke or problems with your blood circulation
- Have serious liver problems
- Have taken any of the following medicines in the last 24 hours: other “triptans” like almotriptan (AXERT®), eletriptan (RELPAX®), frovatriptan (FROVA®), naratriptan (AMERGE®), rizatriptan (MAXALT®), sumatriptan (IMITREX®), sumatriptan/naproxen (TREXIMET); ergotamines like BELLERGAL-S® , CAFERGOT® , ERGOMAR® , WIGRAINE®; dihydroergotamine like D.H.E. 45® or MIGRANAL®; or methysergide (SANSERT®). These medications have side effects similar to zolmitriptan orally disintegrating tablets.
- Have taken monoamine oxidase (MAO) inhibitors such as phenelzine sulfate (NARDIL®) or tranylcypromine sulfate (PARNATE®) for depression or other conditions within the last 2 weeks.
- Are allergic to zolmitriptan orally disintegrating tablets or any of its ingredients. The active ingredient is zolmitriptan. The inactive ingredients are listed at the end of this leaflet.

Tell your doctor about all the medicines you take or plan to take, including prescription and non-prescription medicines, supplements, and herbal remedies.

Tell your doctor if you are sensitive to phenylalanine, which can be found in the artificial sweetener aspartame. Zolmitriptan orally disintegrating tablets contain phenylalanine.

Tell your doctor if you are taking selective serotonin reuptake inhibitors (SSRIs) or serotonin norepinephrine reuptake inhibitors (SNRIs), two types of drugs for depression or other disorders. Common SSRIs are CELEXA® (citalopram HBr), LEXAPRO® (escitalopram oxalate), PAXIL® (paroxetine), PROZAC® (fluoxetine), SYMBYAX® (olanzapine/fluoxetine), ZOLOFT® (sertraline), SARAFEM® (fluoxetine) and LUVOX® (fluvoxamine). Common SNRIs are CYMBALTA® (duloxetine) and EFFEXOR® (venlafaxine). Your doctor will decide if you can take zolmitriptan orally disintegrating tablets with your other medicines.

Tell your doctor if you know that you have any of the following: risk factors for heart disease like high cholesterol, diabetes, smoking, obesity (overweight), menopause, or a family history of heart disease or stroke.

Tell your doctor if you are pregnant or plan to become pregnant. It is not known if zolmitriptan will harm your unborn baby.

Tell your doctor if you are breastfeeding or plan to breastfeed. It is not known if zolmitriptan passes into your breast milk. Talk to your doctor about the best way to feed your baby while using zolmitriptan orally disintegrating tablets.

How should I take zolmitriptan orally disintegrating tablets?

- Take zolmitriptan orally disintegrating tablets exactly as your doctor tells you to take it. Your doctor will tell you how many zolmitriptan orally disintegrating tablets to take and when to take them.
- If you take zolmitriptan orally disintegrating tablets, do not remove the tablet from the blister pack until you are ready to take your medicine.
- You do not need to take any liquids with your zolmitriptan orally disintegrating tablets.
- Take zolmitriptan orally disintegrating tablets whole.
- Place zolmitriptan orally disintegrating tablets on your tongue, where it will dissolve.
- Safely throw away any unused tablets or pieces of tablets that have been removed from the blister packaging.
- If your headache comes back after your first dose, you may take a second dose any time after 2 hours of taking the first dose. For any attack where the first dose did not work, do not take a second dose without talking with your doctor. Do not take more than a total of 10 mg of zolmitriptan (tablets or spray combined) in any 24 hour period. If you take too much medicine, contact your doctor, hospital emergency department, or poison control center right away.

What are the possible side effects of zolmitriptan orally disintegrating tablets?

Zolmitriptan orally disintegrating tablets are generally well tolerated. As with any medicine, people taking zolmitriptan orally disintegrating tablets may have side effects. The side effects are usually mild and do not last long.

The most common side effects of zolmitriptan orally disintegrating tablets are:

- pain, pressure or tightness in the neck, throat or jaw
- dizziness
- tingling or other abnormal sensations
- tiredness
- drowsiness
- feeling warm or cold
- nausea
- feeling of tightness or heaviness in other areas of the body
- dry mouth

In very rare cases, patients taking triptans may experience serious side effects, such as heart attacks, high blood pressure, stroke, or serious allergic reactions. Extremely rarely, patients have died. Call your doctor right away if you have any of the following problems after taking zolmitriptan orally disintegrating tablets:

- severe tightness, pain, pressure or heaviness in your chest, throat, neck, or jaw
- shortness of breath or wheezing
- sudden or severe stomach pain
- hives; tongue, mouth, or throat swelling
- problems seeing
- unusual weakness or numbness

Some people may have a reaction called serotonin syndrome, which can be life-threatening, when they use zolmitriptan orally disintegrating tablets. In particular, this reaction may occur when they use zolmitriptan orally disintegrating tablets together with certain types of antidepressants known as SSRIs or SNRIs. Symptoms may include mental changes (hallucinations, agitation, coma), fast heartbeat, changes in blood pressure, high body temperature or sweating, tight muscles, trouble walking, nausea, vomiting, and diarrhea. Call your doctor immediately if you have any of these symptoms after taking zolmitriptan orally disintegrating tablets.

This is not a complete list of side effects. Talk to your doctor if you develop any symptoms that concern you.

Call your doctor for medical advice about side effects. You may report side effects to FDA at 1-800-FDA-1088.

What to do in case of an overdose?

Call your doctor or poison control center or go to the nearest hospital emergency room.

General advice about zolmitriptan orally disintegrating tablets

Medicines are sometimes prescribed for conditions that are not mentioned in patient information leaflets. Do not use zolmitriptan orally disintegrating tablets for a condition for which they were not prescribed. Do not give zolmitriptan orally disintegrating tablets to other people, even if they have the same symptoms as you. People may be harmed if they take medicines that have not been prescribed for them.

This leaflet summarizes the most important information about zolmitriptan orally disintegrating tablets. If you would like more information about zolmitriptan orally disintegrating tablets, talk to your doctor. You can ask your doctor or pharmacist for information on zolmitriptan orally disintegrating tablets that is written for healthcare professionals.

You can also call 1 (888) 721-7115 or visit our website at www.glenmarkpharma-us.com.

What are the ingredients in zolmitriptan orally disintegrating tablets?

Active ingredient: zolmitriptan

Inactive ingredients: aspartame, colloidal silicon dioxide, crospovidone, magnesium stearate, mannitol, microcrystalline cellulose, peppermint flavor and talc. The peppermint flavor contains corn starch.

Store zolmitriptan orally disintegrating tablets at 20°C to 25°C (68°F to 77°F); [see USP Controlled Room Temperature] and away from children.

Protect from light and moisture. Discard when expired.

Other brands mentioned are trademarks of their respective owners and are not trademarks of Glenmark Pharmaceuticals Limited. The makers of these brands are not affiliated with Glenmark Pharmaceuticals Limited or its products.

Distributed by:

Glenmark Pharmaceuticals Inc., USA

Elmwood Park, NJ 07407

Questions? 1 (888) 721-7115

www.glenmarkpharma-us.com

June 2025

Package/Label Display Panel

NDC 68462-499-76
Zolmitriptan Orally Disintegrating Tablets, 2.5 mg
Carton Label – 6 unit-dose tablets

Package/Label Display Panel

NDC 68462-500-33
Zolmitriptan Orally Disintegrating Tablets, 2.5 mg
Carton Label – 3 unit-dose tablets